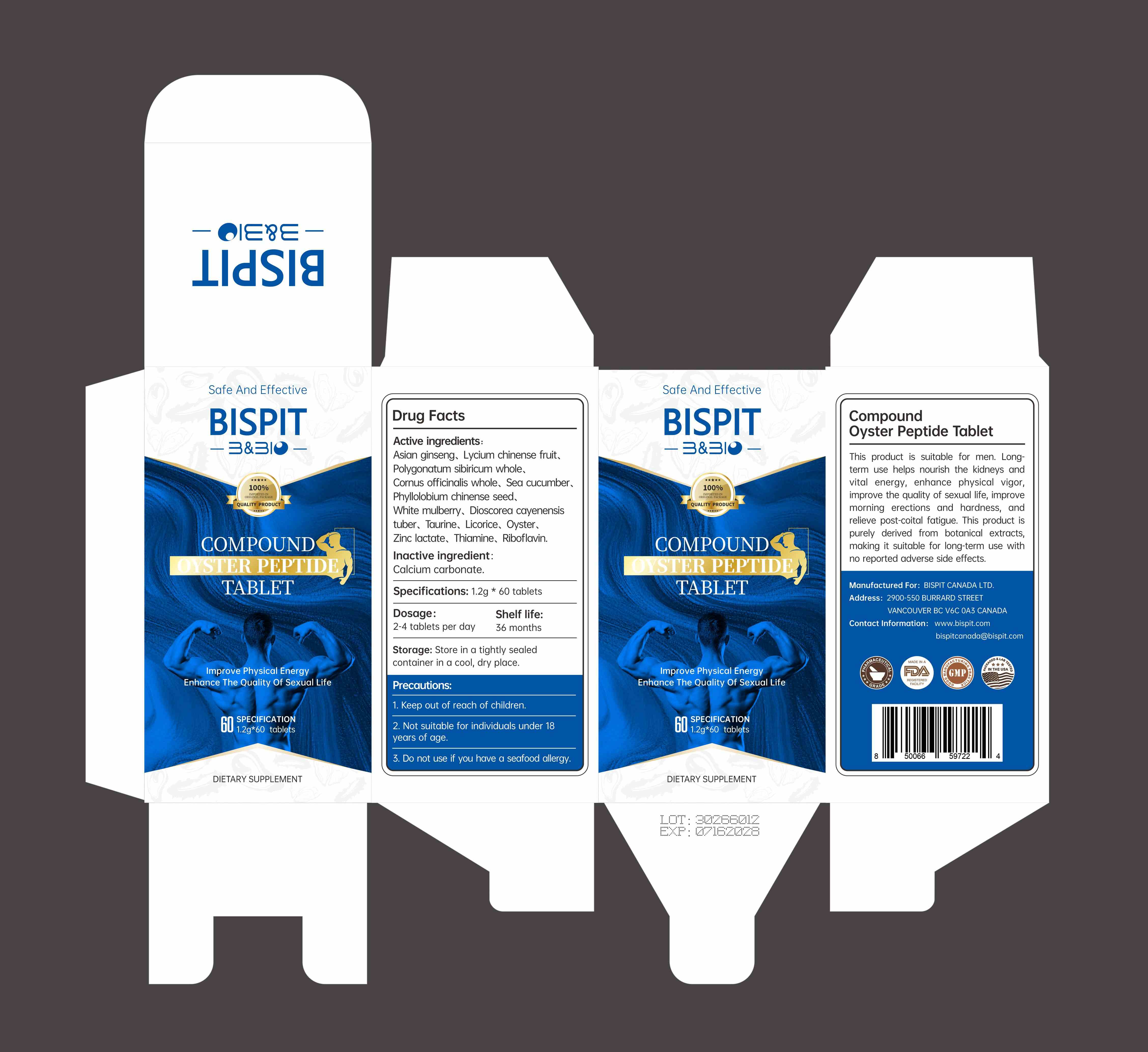 DRUG LABEL: COMPOUND OYSTER PEPTIDE
NDC: 85631-004 | Form: CAPSULE
Manufacturer: Bispit Canada Ltd.
Category: homeopathic | Type: HUMAN OTC DRUG LABEL
Date: 20250803

ACTIVE INGREDIENTS: LYCIUM CHINENSE FRUIT 270 mg/1.2 g; ASIAN GINSENG 180 mg/1.2 g; LICORICE 24 mg/1.2 g; POLYGONATUM SIBIRICUM WHOLE 90 mg/1.2 g; PHYLLOLOBIUM CHINENSE SEED 72 mg/1.2 g; RIBOFLAVIN 0.24 mg/1.2 g; ZINC LACTATE 5.16 mg/1.2 g; TAURINE 30 mg/1.2 g; THIAMINE 0.6 mg/1.2 g; CORNUS OFFICINALIS WHOLE 180 mg/1.2 g; SEA CUCUMBER, UNSPECIFIED 120 mg/1.2 g; DIOSCOREA CAYENENSIS TUBER 96 mg/1.2 g; WHITE MULBERRY 72 mg/1.2 g; OYSTER, UNSPECIFIED 12 mg/1.2 g
INACTIVE INGREDIENTS: CALCIUM CARBONATE

85631-004-01

ACTIVE INGREDIENT

ASIAN GINSENG
LYCIUM CHINENSE FRUIT
POLYGONATUM SIBIRICUM WHOLE
CORNUS OFFICINALIS WHOLE
SEA CUCUMBER, UNSPECIFIED
PHYLLOLOBIUM CHINENSE SEED
WHITE MULBERRY
DIOSCOREA CAYENENSIS TUBER
1EQV5MLY3D
LICORICE
OYSTER
ZINC LACTATE
THIAMINE
RIBOFLAVIN

PURPOSE

lmprove Physical EnergyEnhance The Quality Of Sexual Life

WARNINGS

Not suitable for individuals under 18years of age

Do not use if you have a seafood allergy.

Keep out of reach of children.

Do not use if you have a seafood allergy

WHEN USING

This productisuatle for men.Longlem use helps nourish the kidneys andal energy enhance physical vigorimprove thequalty of sexualfe,improvemornimg erecions and hardnes,andeeve postcoila
fatigue. This product ispurely derived from botanical extracts,making it suitable for long-term use withno reported adverse side effects.

Dosage:2-4 tablets per day

INDICATIONS AND USAGE

Thisproductisuable for men.Long em use helpsnouish the kidneys antvila energyenhancephyskcal igoimprowve thequalty of sexual le,imprvemornimg erecions and hardnes,andeeve postcoita
fatigue. This product ispurely derived from botanical extracls, making it suitable for long-term use withno reported adverse side effects

INACTIVE INGREDIENT

CALCIUM CARBONATE